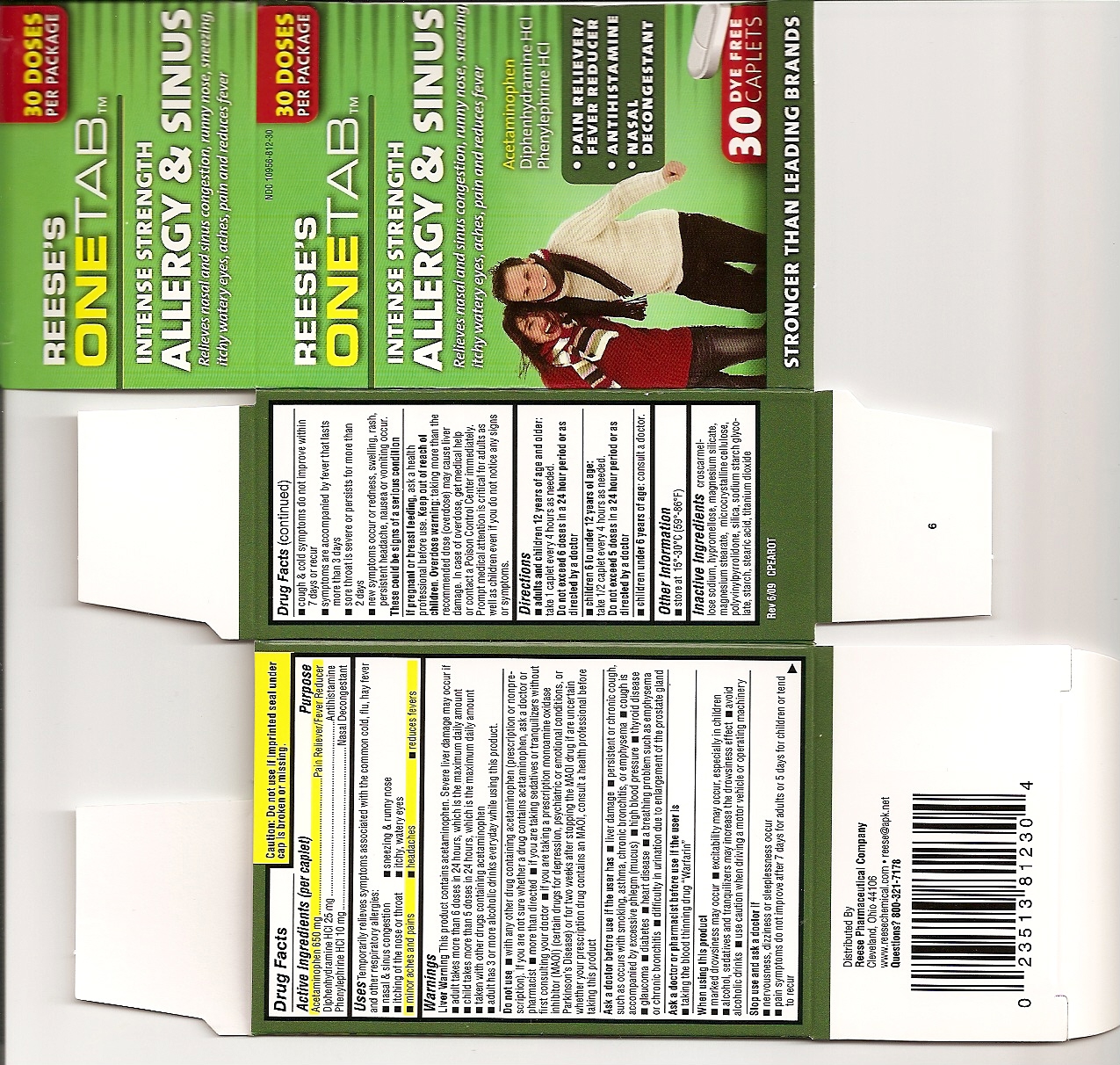 DRUG LABEL: REESES ONETAB ALLERGY AND SINUS
NDC: 10956-812 | Form: TABLET
Manufacturer: REESE PHARMACEUTICAL CO.
Category: otc | Type: HUMAN OTC DRUG LABEL
Date: 20100818

ACTIVE INGREDIENTS: ACETAMINOPHEN 650 mg/1 1; DIPHENHYDRAMINE  HYDROCHLORIDE 25 mg/1 1; PHENYLEPHRINE  HYDROCHLORIDE 10 mg/1 1
INACTIVE INGREDIENTS: hypromellose; magnesium silicate; magnesium stearate; CELLULOSE, MICROCRYSTALLINE; TITANIUM DIOXIDE; CROSCARMELLOSE SODIUM; STEARIC ACID 

DRUG FACTS

ACTIVE INGREDIENT

Acetaminophen 650 mg
Diphenhydramine Hydochloride 25 mg
Phenylephrine Hydrochloride 10 mg

INACTIVE INGREDIENT

croscarmellose sodium,htpromellose,magnesium silicate,magnesium stearate,
microcrystalline cellulose,polyvinylpyrrolidone,silica,sodium starch glycolate,starch,
stearic acid,titanium dioxide.

PURPOSE

Pain Reliever/Fever Reducer
Antihistamine/Cough Suppressant
Nasal Decongestant

INDICATIONS AND USAGE

Temporarily relieves symptoms associated with the common cold, flu, hay fever
and other respiratory allergies
nasal and sinus congestion
itching of the nose or throat
minor aches and pains
sneezing and runny nose
itchy, watery eyes
headaches

WARNINGS

LIVER WARNING : THIS PRODUCT CONTAINS ACETAMINOPHEN.SEVERE LIVER
DAMAGE MAY OCCUR IF ADULT TAKES MORE THAN 6 DOSES IN 24 HOURS
WHICH IS THE MAXIMUM DAILY AMOUNT, A CHILD TAKES MORE THAN 5 DOSES
IN 24 HOURS , WHICH IS THE MAXIMUM DAILY AMOUNT , TAKEN WITH OTHER
DRUGS CONTAINING ACETAMINOPHEN ,ADULT HAS 3 OR MORE ALCOHOLIC DRINKS
EVERYDAY WHILE USING THIS PRODUCT

Directions
adults and children 12 years of age and older: take 1 caplet every 4 hours as needed.
Do not exceed 6 doses In a 24 hour period or as directed by a doctor
children 6 to under 12 years of age: take 1/2 caplet every 4 hours as needed.
Do not exceed 5 doses In a 24 hour period or as directed by a doctor
children under 6 years of ago: consult a doctor

KEEP OUT OF REACH OF CHILDREN

Do not use _ with any other drug containing acetaminophen (prescription or nonpreescription). If you are not sure whether a drug contains acetaminophen, ask a doctor or pharmacist _ more than directed _ if you are taking sedatives or tranquilizers without first consulting your doctor _ if you are taking a prescription monoamine oxidase inhibitor (MAOI) (certain drugs for depression, psychiatric or emotional conditions, or Parkinson's Disease) or for two weeks after stopping the MAD I drug if are uncertain whether your prescription drug contains an MAOI, consuit a health professional before taking this product

Ask a doctor before use if the user has liver damage persistent or chronic cough, such as occurs with smoking, asthma, chronic bronchitis, or emphysema, cough is accompanied by excessive phlegm (mucus), high blood pressure, thyroid disease, glaucoma, diabetes, heart disease, a breathing problem such as emphysema or chronic bronchitis, difficulty In urination due to enlargement of the prostate gland

Ask a doctor or pharmacist before use if the user is taking the blood thinning drug "Warfarin"

When using this product
marked drowsiness may occur _ excitability may occur, especially in children
alcohol, sedatives and tranquilizers may increase the drowsiness effect _ avoid alcoholic drinks _ use caution when driving a motor vehicle or operating machinery

Stop use and ask a doctor if
- nervousness, dizziness or sleeplessness occur,
- pain symptoms do not improve after 7 days for adults or 5 days for children orlend to recur
_ cough and cold symptoms do not improve within 7 days or recur
_ symptoms are accompanied by fever that lasts more than 3 days
_ sore throat is severe or persists for more than 2 days
_ new symptoms occur or redness, swelling, rash, persistent headache, nausea or vomiting occur.
These could be signs of a serious condition

PREGNANCY OR BREAST FEEDING

If pregnant or breast feeding, ask a health professional before use.

OVERDOSAGE

In case of overdose, get medical help or contact a Poison Control Center immediately. Prompt medical attention is critical for adults as well as children even if you do not notice any signs or symptoms.

Other Information
_ store at 15'-30'C (59'-86'F)